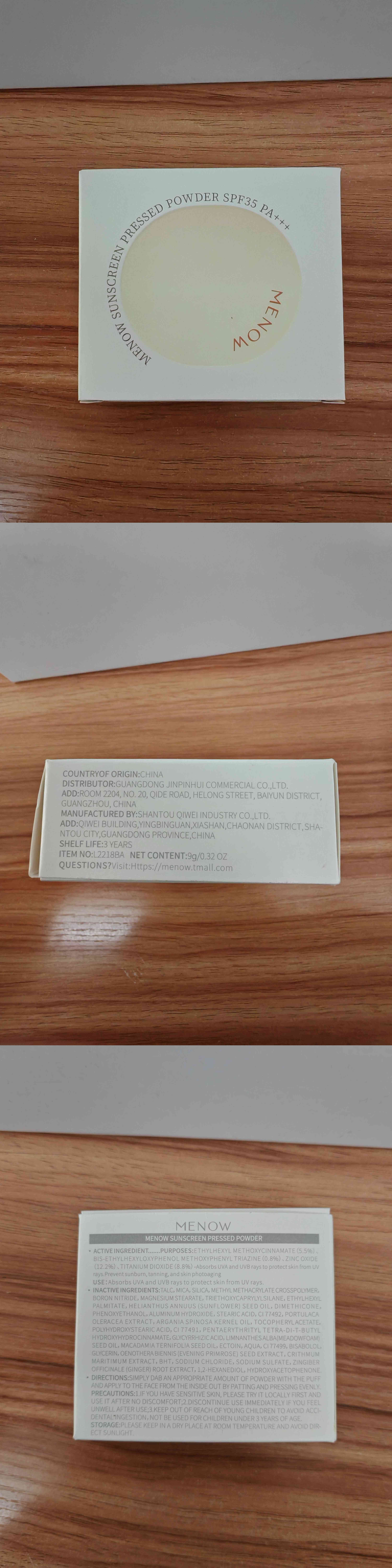 DRUG LABEL: MENOW SUNSCREEN
NDC: 85138-101 | Form: POWDER
Manufacturer: SHANTOU QIWEI INDUSTRY CO.,LTD
Category: otc | Type: HUMAN OTC DRUG LABEL
Date: 20250117

ACTIVE INGREDIENTS: BIS-ETHYLHEXYLOXYPHENOL METHOXYPHENYL TRIAZINE 0.772 g/100 g; ZINC OXIDE 11.89646 g/100 g; ETHYLHEXYL METHOXYCINNAMATE 5.83874 g/100 g; TITANIUM DIOXIDE 8.02712 g/100 g
INACTIVE INGREDIENTS: MAGNESIUM STEARATE; CI 77492; ETHYLHEXYL PALMITATE; BHT; SODIUM SULFATE; TRIETHOXYCAPRYLYLSILANE; GINGER; 1,2-HEXANEDIOL; ALUMINUM HYDROXIDE; HELIANTHUS ANNUUS (SUNFLOWER) SEED OIL; SODIUM CHLORIDE; TALC; DIMETHICONE; STEARIC ACID; PURSLANE; METHYL METHACRYLATE/GLYCOL DIMETHACRYLATE CROSSPOLYMER; LIMNANTHES ALBA (MEADOWFOAM) SEED OIL; ALPHA-TOCOPHEROL ACETATE; PHENOXYETHANOL; CRITHMUM MARITIMUM; HYDROXYACETOPHENONE; BORON NITRIDE; POLYHYDROXYSTEARIC ACID (2300 MW); OENOTHERA BIENNIS (EVENING PRIMROSE) OIL; ARGANIA SPINOSA KERNEL OIL; CI 77491; PENTAERYTHRITYL TETRA-DI-T-BUTYL HYDROXYHYDROCINNAMATE; MACADAMIA TERNIFOLIA SEED OIL; GLYCYRRHIZIC ACID; AQUA; CI 77499; SILICA; MICA; GLYCERIN; ECTOIN; BISABOLOL

ACTIVE INGREDIENT

Active ingredients: ETHYLHEXYL METHOXYCINNAMATE(5.83874g/100g), BIS-ETHYLHEXYLOXYPHENOL METHOXYPHENYL TRIAZINE(0.772g/100g), ZINC OXIDE(11.89646/100g), TITANIUM DIOXIDE(8.02712g/100g)

PURPOSE

Use to Absorbs UVA and UVB rays to protect skin from UV rays.Prevent sunburn, tanning, and skin photoaging

INDICATIONS AND USAGE

Indications & usage section:SUNSCREEN PRESSED POWDER,SETTING MAKEUP WHILE PROTECTING AGAINST UVA/UVB

Warnings:

1.IF YOU HAVE SENSITIVE SKIN, PLEASE TRY IT LOCALLY FIRST ANDUSE IT AFTER NO DISCOMFORT;

2.DISCONTINUE USE IMMEDIATELY IF YOU FEELUNWELL AFTER USE;

3.KEEP OUT OF REACH OF YOUNG CHILDREN TO AVOID ACCI.DENTAL INGESTION, NOT BE USED FOR CHILDREN UNDER 3 YEARS OF AGE.

DIRECTIONS:

SIMPLY DAB AN APPROPRIATE AMOUNT OF POWDER WITH THE PUFF AND APPLY TO THE FACE FROM THE INSIDE OUT BY PATTING AND PRESSING EVENLY.

Inactive ingredients:

TALC, MICA, SILICA, METHYL METHACRYLATE CROSSPOLYMER, BORON NITRIDE, MAGNESIUM STEARATE, TRIETHOXYCAPRYLYLSILANE, ETHYLHEXYL PALMITATE, HELIANTHUS ANNUUS (SUNFLOWER) SEED OIL, DIMETHICONE, PHENOXYETHANOL, ALUMINUM HYDROXIDE, STEARIC ACID, CI 77492, PORTULACA OLERACEA EXTRACT, ARGANIA SPINOSA KERNEL OIL, TOCOPHERYL ACETATE, POLYHYDROXYSTEARIC ACID, CI 77491, PENTAERYTHRITYL TETRA-DI-t-BUTYL HYDROXYHYDROCINNAMATE, GLYCYRRHIZIC ACID, LIMNANTHES ALBA (MEADOWFOAM) SEED OIL, MACADAMIA TERNIFOLIA SEED OIL, ECTOIN, AQUA, CI 77499, BISABOLOL, GLYCERIN, OENOTHERA BIENNIS (EVENING PRIMROSE) SEED EXTRACT, CRITHMUM MARITIMUM EXTRACT, BHT, SODIUM CHLORIDE, SODIUM SULFATE, ZINGIBER OFFICINALE (GINGER) ROOT EXTRACT, 1,2-HEXANEDIOL, HYDROXYACETOPHENONE

KEEP OUT OF REACH OF CHILDREN

KEEP OUT OF REACH OF YOUNG CHILDREN TO AVOID ACCIDENTAL INGESTION,NOT BE USED FOR CHILDREN UNDER 3YEARS OF AGE.

OTHER SAFETY INFORMATION

PLEASE KEEP IN A DRY PLACE AT ROOM TEMPERATURE AND AVOID DIR-ECT SUNLIGHT.

See label